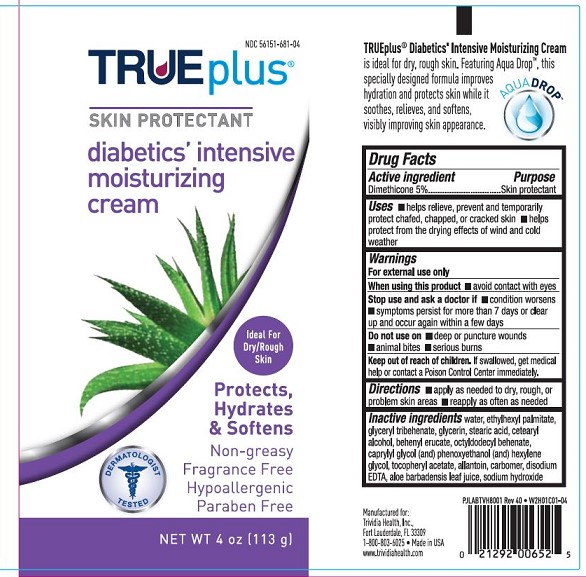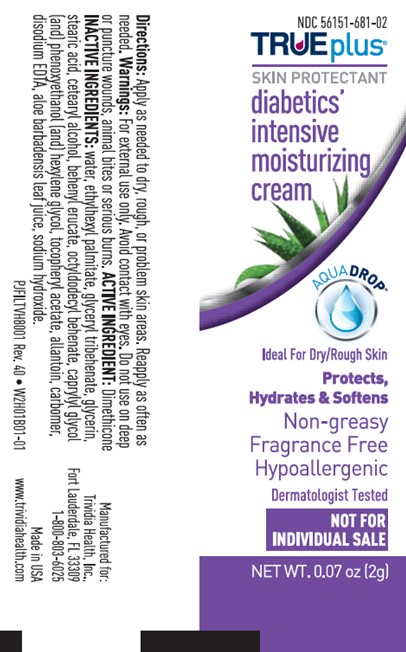 DRUG LABEL: Diabetics intensive moisturizing
NDC: 56151-681 | Form: CREAM
Manufacturer: Trividia Health, Inc.
Category: otc | Type: HUMAN OTC DRUG LABEL
Date: 20220216

ACTIVE INGREDIENTS: DIMETHICONE 5 g/100 g
INACTIVE INGREDIENTS: WATER; ALLANTOIN; GLYCERIN; ALOE; ETHYLHEXYL PALMITATE; BEHENYL ERUCATE; STEARIC ACID; CETOSTEARYL ALCOHOL; SODIUM HYDROXIDE; ALPHA-TOCOPHEROL ACETATE; CARBOMER INTERPOLYMER TYPE A (55000 CPS); CAPRYLYL GLYCOL; PHENOXYETHANOL; HEXYLENE GLYCOL; EDETATE DISODIUM; TRIBEHENIN; OCTYLDODECYL BEHENATE

Diabetics intensive moisturizing

Active Ingredients

Dimethicone 5%

Purpose

Skin protectant

Uses

Helps relieve, prevent and temporarily protect chafed, chapped, or cracked skin. helps protect from the drying effects of wind and cold weather.

Warnings

For external use only

When using this product

avoid contact with eyes

Stop use and ask a doctor if

condition worsens, symptoms persist for more than 7 days or clear up and occur again within a few days

Do not use on

deep or puncture wounds, animal bites, serious burns

Keep out of reach of children

If swallowed, get medical help or contact a Poison Control Center immediately

Directions

apply as needed to dry, rough, or problem skin areas, reapply as often as needed

Inactive ingredients

water, ethylhexyl palmitate, glyceryl tribehenate, glycerin, stearic acid, cetearyl alcohol, behenyl erucate, octyldodecyl behenate, caprylyl glycol, phenoxyethanol, hexylene glycol, tocopheryl acetate, allantoin, carbomer, disodium EDTA, aloe barbadensis leaf juice, sodium hydroxide